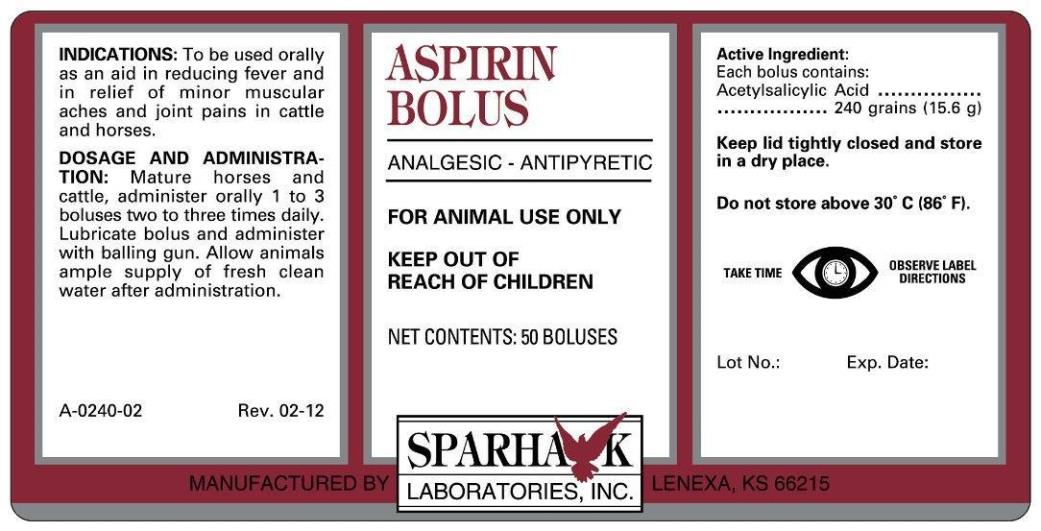 DRUG LABEL: ASPIRIN 
NDC: 58005-240 | Form: TABLET
Manufacturer: Sparhawk Laboratories, Inc.
Category: animal | Type: OTC ANIMAL DRUG LABEL
Date: 20210416

ACTIVE INGREDIENTS: ASPIRIN 15.6 g/1 1

ASPIRIN BOLUS

INDICATIONS AND USAGE

ANALGESIC-ANTIPYRETIC

FOR ANIMAL USE ONLY

KEEP OUT OF REACH OF CHILDREN

INDICATIONS

To be used orally as an aid in reducing fever and in relief of minor muscular aches and joint pains in cattle and horses.

DOSAGE AND ADMINISTRATION

Mature Horses and Cattle, administer orally 1 to 3 Boluses two to three times daily. Lubricate bolus and administer with balling gun. Allow Animals ample supply of fresh clean water after administration.

Active Ingredients

Each bolus contains:
Acetylsalicylic Acid..........240 grains (15.6 g)

STORAGE AND HANDLING

Keep lid tightly closed and store in a dry place.

Do not store above 30oC (86oF).

TAKE TIME OBSERVE LABEL DIRECTIONS